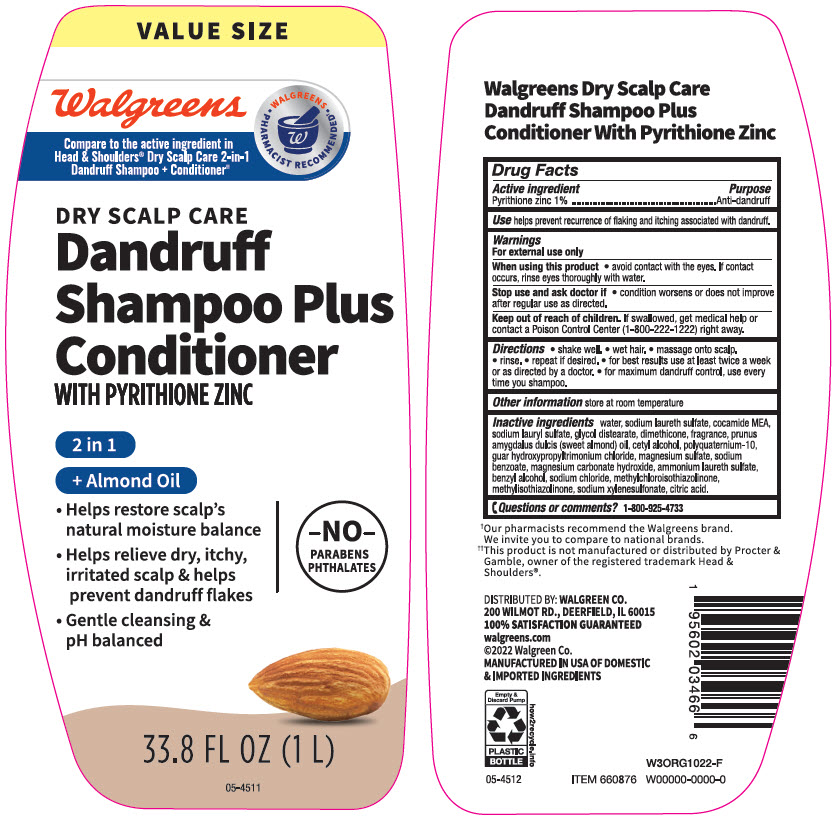 DRUG LABEL: Walgreens Dandruff Plus Conditioner 2 in 1 Dry Scalp
NDC: 0363-4666 | Form: SHAMPOO
Manufacturer: Walgreen Company
Category: otc | Type: HUMAN OTC DRUG LABEL
Date: 20241104

ACTIVE INGREDIENTS: Pyrithione Zinc 10 mg/1 mL
INACTIVE INGREDIENTS: Water; SODIUM LAURETH-3 SULFATE; COCO MONOETHANOLAMIDE; Sodium Lauryl Sulfate; GLYCOL DISTEARATE; Dimethicone; ALMOND OIL; Cetyl Alcohol; POLYQUATERNIUM-10 (30000 MPA.S AT 2%); GUAR HYDROXYPROPYLTRIMONIUM CHLORIDE (1.7 SUBSTITUENTS PER SACCHARIDE); MAGNESIUM SULFATE, UNSPECIFIED FORM; Sodium Benzoate; Magnesium Carbonate Hydroxide; AMMONIUM LAURETH-5 SULFATE; Benzyl Alcohol; Sodium Chloride; Methylchloroisothiazolinone; Methylisothiazolinone; Sodium Xylenesulfonate; CITRIC ACID MONOHYDRATE

Walgreens Dandruff Shampoo Plus Conditioner 2 in 1 Dry Scalp
Anti-dandruff

Drug Facts

Active ingredient

Pyrithione Zinc 1%

Purpose

Anti-dandruff

Use

helps prevent recurrence of flaking and itching associated with dandruff.

Warnings

For external use only

When using this product

- avoid contact with the eyes. If contact occurs, rinse eyes thoroughly with water.

Stop use and ask a doctor if

- condition worsens or does not improve after regular use as directed.

Keep out of reach of children. If swallowed, get medical help or contact a Poison Control Center (1-800-222-1222) right away.

Directions

- shake well
- wet hair
- massage onto scalp
- rinse
- repeat if desired
- for best results use at least twice a week or as directed by a doctor
- for maximum dandruff control, use every time you shampoo.

Other information

store at room temperature

Inactive ingredients

water, sodium laureth sulfate, cocamide MEA, sodium lauryl sulfate, glycol distearate, dimethicone, fragrance, prunus amygdalus dulcis (sweet almond) oil, cetyl alcohol, polyquaternium-10, guar hydroxypropyltrimonium, magnesium sulfate, sodium benzoate, magnesium carbonate hydroxide, ammonium laureth sulfate, benzyl alcohol, sodium chloride, methylchloroisothiazolinone, methylisothiazolinone, sodium xylenesulfonate, citric acid.

Questions or Comments?

1-800-925-4733

DISTRIBUTED BY: WALGREEN CO.
200 WILMOT RD., DEERFIELD, IL 60015

PRINCIPAL DISPLAY PANEL - 1 L Bottle Label

VALUE SIZE

Walgreens

Compare to the active ingredient in
Head & Shoulders® Dry Scalp Care 2-in-1
Dandruff Shampoo + Conditioner††

WALGREENS
• PHARMACIST RECOMMENDED†•

DRY SCALP CARE
Dandruff
Shampoo Plus
Conditioner
WITH PYRITHIONE ZINC

2 in 1
+ Almond Oil

- Helps restore scalp's
  natural moisture balance
- Helps relieve dry, itchy,
  irritated scalp & helps
  prevent dandruff flakes
- Gentle cleansing &
  pH balanced

-NO-
PARABENS
PHTHALATES

33.8 FL OZ (1 L)

05-4511